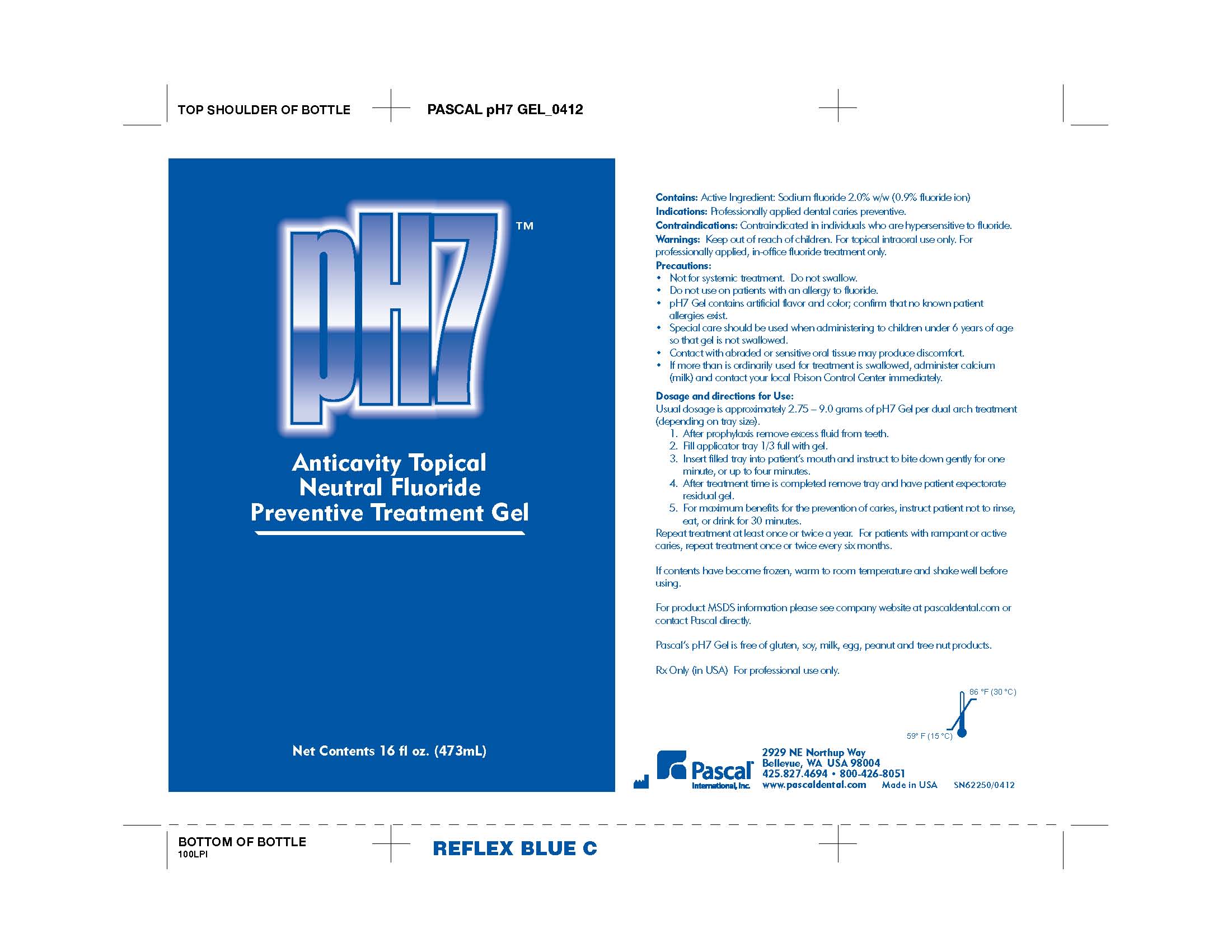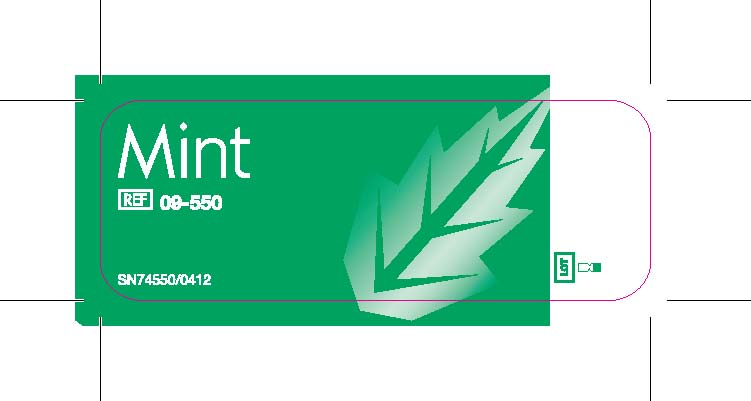 DRUG LABEL: pH7 Gel Mint
NDC: 10866-0093 | Form: GEL
Manufacturer: Pascal Company, Inc.
Category: prescription | Type: HUMAN PRESCRIPTION DRUG LABEL
Date: 20150326

ACTIVE INGREDIENTS: Sodium Fluoride 9.05 mg/1 g

PACKAGE LABEL

pH7 Anticavity Topical Neutral Fluoride Preventive Treatment Gel

Mint

Contains:

Active Ingredient: Sodium Fluoride 2.0% w/w /0.9% fluoride ion

Indications

Professionally applied dental caries preventive.

Contraindications

Contraindicated in individuals who are hypersensitive to fluoride.

Warnings and Precautions

Keep out of reach of children. For topical intraoral use only. For professionally applied, in-office fluoride treatment only.

- Not for systemic treatement. Do not swallow.
- Do not use on patients with an allergy to fluoride
- pH7 Gel contains artificial flavor and color; confirm that no known patient allergies exist.
- Special care should be used when administering to children under 6 years of age so that gel is not swallowed.
- Contact with abraded or sensitive oral tissue may produce discomfort.
- If more than is ordinarily used for treatment is swallowed, adminster calcium such as milk and contact your local Poison Control Center immediately.

Dosage and Directions for Use

Usual dosage is approximately 2.75-9.0 grams of pH7 Gel per dual arch treatment depending on tray size

1. After prophylaxis remove excess fluid from teeth.
2. Fill applicator tray 1/3 full with gel.
3. Insert filled tray into patient's mouth and instruct to bite down gently for one minute or up to four minutes.
4. After treatment time is completed remove tray and have patient expectorate residual gel.
5. For maximum benefits for the prevention of caries, instruct patient not to rinse, eat or drink for 30 minutes.

Repeat treatment at least once or twice a year. For patients with rampant or active caries, repeat treatment once or twice every six months.

If contents have become frozen, warm to room temperature and shake well before using.

Other Safety Information

For product MSDS information please see company website at pascaldental.com or contact Pascal directly.

pH7 Gel is free of gluten, soy, milk, egg, peanut and tree nut products.

Rx Only in USA For Professional Use only.